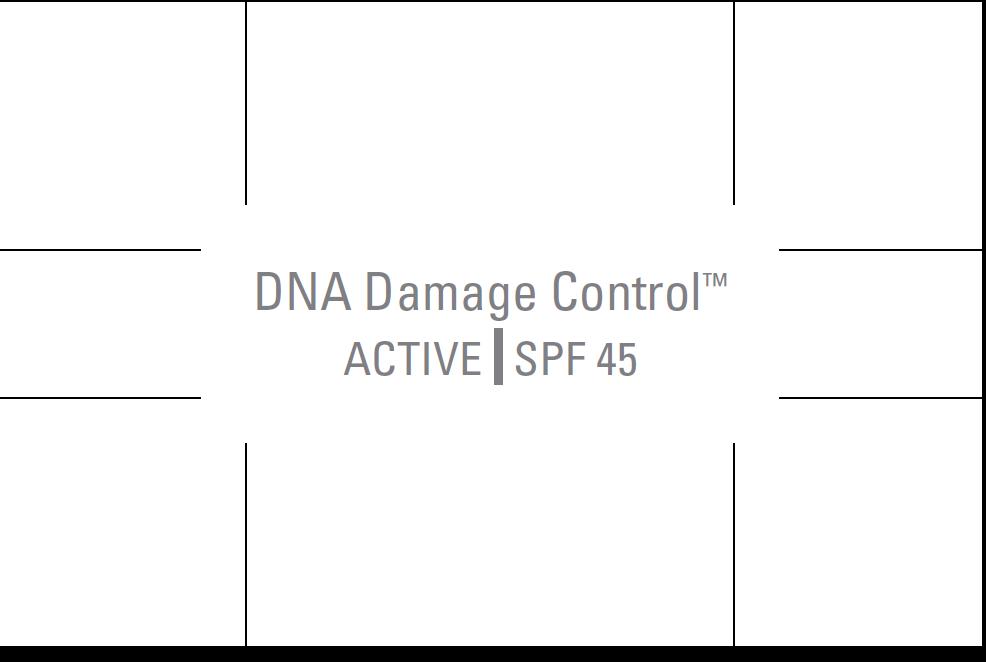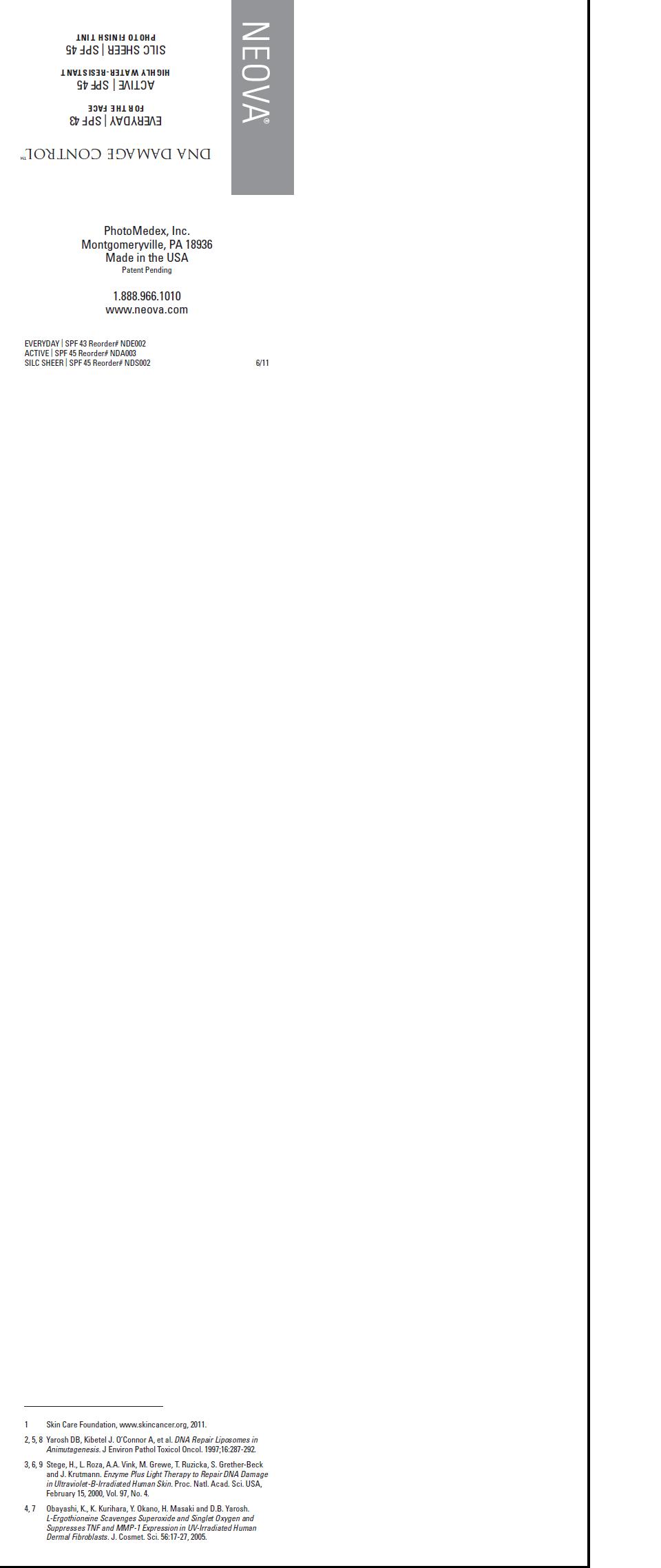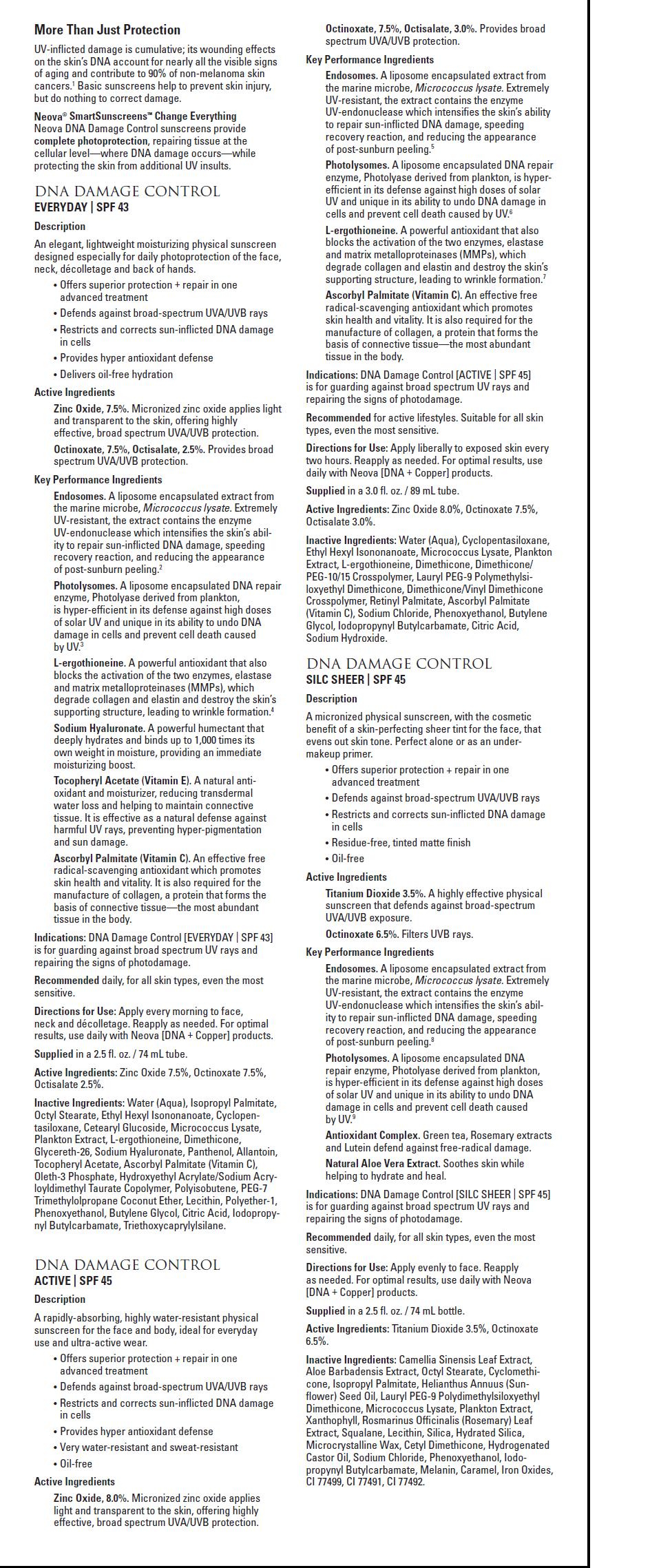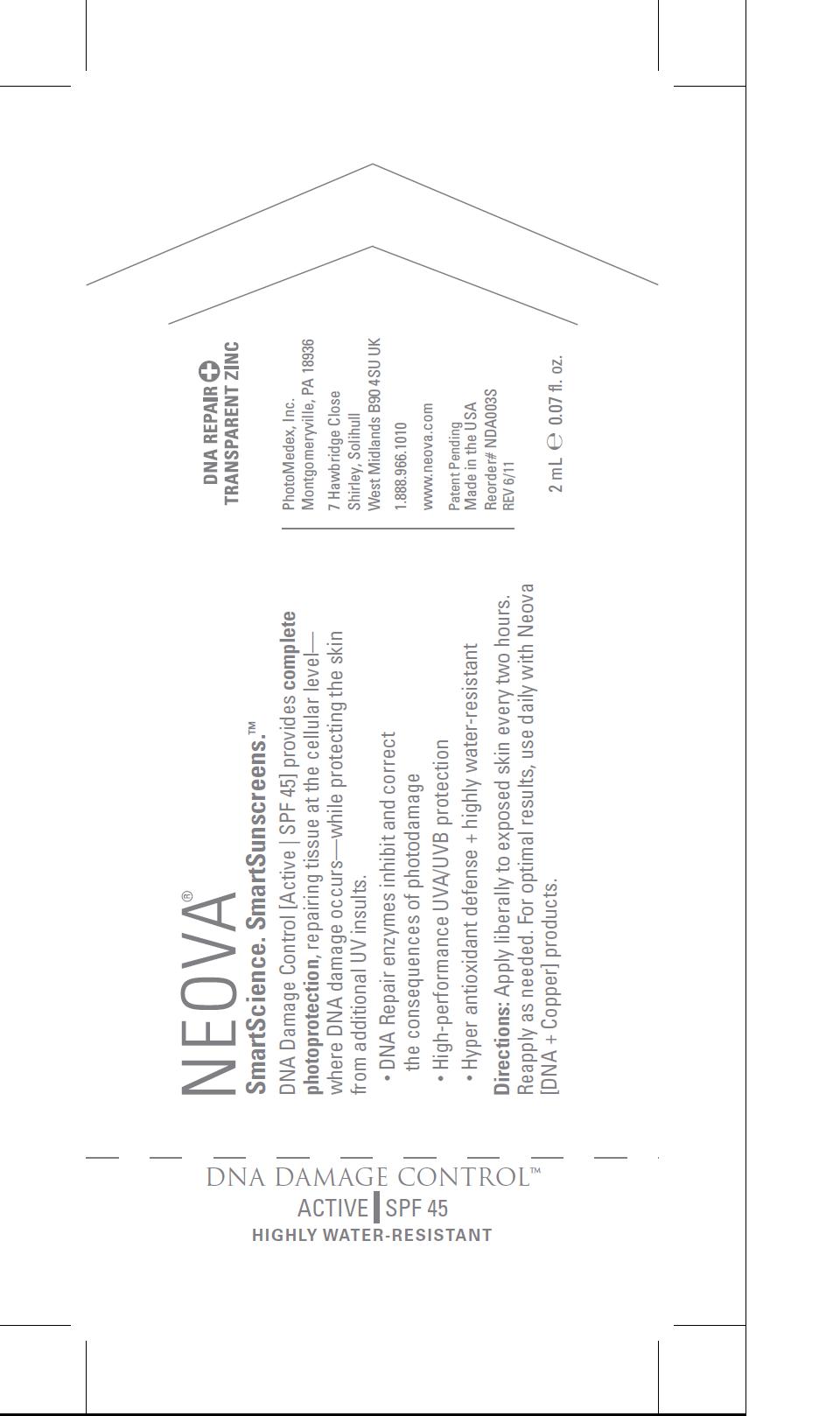 DRUG LABEL: Neova DNA Damage Control - Active 
NDC: 62362-129 | Form: EMULSION
Manufacturer: PhotoMedex, Inc.
Category: otc | Type: HUMAN OTC DRUG LABEL
Date: 20120106

ACTIVE INGREDIENTS: Zinc Oxide 8 mL/100 mL; Octinoxate 7.5 mL/100 mL; Octisalate 3 mL/100 mL
INACTIVE INGREDIENTS: Water; Cyclomethicone 5; Ethylhexyl Isononanoate; Micrococcus Luteus; Ergothioneine; Dimethicone; Vitamin A Palmitate; Ascorbyl Palmitate; Sodium Chloride; Phenoxyethanol; Butylene Glycol; Iodopropynyl Butylcarbamate; Citric Acid; Sodium Hydroxide

Neova DNA Damage Control - Active SPF 45 - 2mL sample package insert

Directions for use:

Apply liberally to exposed skin every two hours. Reapply as needed. For optimal results, use daily with Neova [DNA + Copper] products.

Supplied

in a 3.0 fl. oz. / 89 mL tube.

Active Ingredients:

Zinc Oxide 8.0%, Octinoxate 7.5%, Octisalate 3.0%.

Inactive Ingredients:

Water (Aqua), Cyclopentasiloxane,
Ethyl Hexyl Isononanoate, Micrococcus Lysate, Plankton
Extract, L-ergothioneine, Dimethicone, Dimethicone/
PEG-10/15 Crosspolymer, Lauryl PEG-9 Polymethylsiloxyethyl
Dimethicone, Dimethicone/Vinyl Dimethicone
Crosspolymer, Retinyl Palmitate, Ascorbyl Palmitate
(Vitamin C), Sodium Chloride, Phenoxyethanol, Butylene
Glycol, Iodopropynyl Butylcarbamate, Citric Acid,
Sodium Hydroxide.

Image of package, pouch, and package insert

AmpuleActive.jpg PouchActive.jpg PkgInsertUniversalpg1.jpg PkgInsertUniversalpg2.jpg